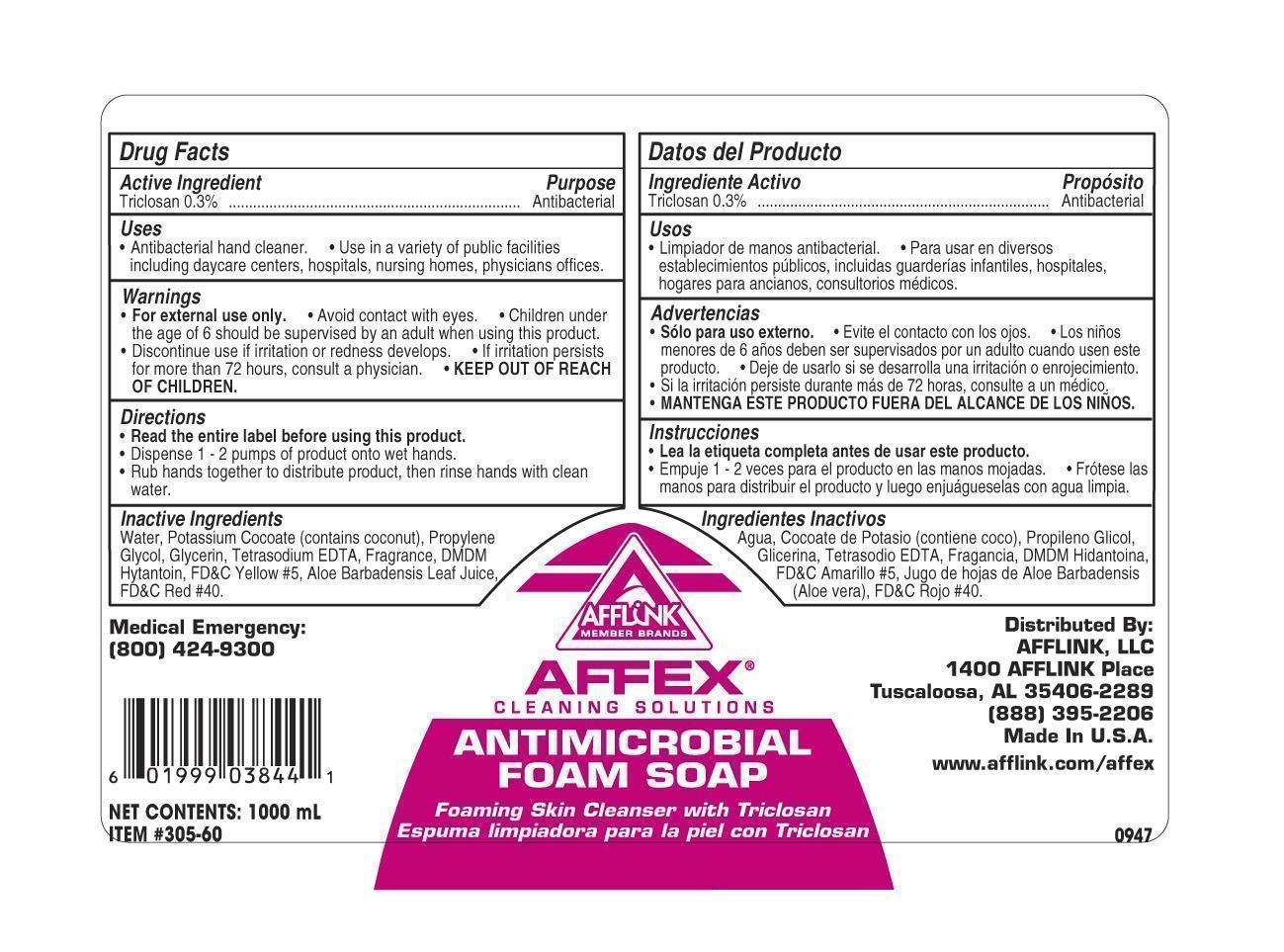 DRUG LABEL: Antimicrobial Foam
NDC: 54057-305 | Form: SOAP
Manufacturer: Afflink, Inc.
Category: otc | Type: HUMAN OTC DRUG LABEL
Date: 20121204

ACTIVE INGREDIENTS: TRICLOSAN 3.0 mg/1 mL
INACTIVE INGREDIENTS: WATER; POTASSIUM COCOATE; PROPYLENE GLYCOL; GLYCERIN; EDETATE SODIUM; DMDM HYDANTOIN; FD&C YELLOW NO. 5; ALOE VERA Leaf; FD&C RED NO. 40

Antimicrobial Foam

Antimicrobial Foam

Active Ingredient

Triclosan 0.30%

Antimicrobial Foam

Uses

- Antibacterial hand cleaner.
- Use in a variet of public facilities including daycare centers, hospitals, nursing homes, physicians offices.

Antimicrobial Foam

Warnings

- For external use only.
- Avoid contact with eyes.
- Children under the age of 6 should be supervised by an adult when using this product.
- Discontinue use is irritation or redness develops.
- If irritation persists for more than 72 hours, consult a physician.
- KEEP OUT OF REACH OF CHILDREN.

Antimicrobial Foam

Directions

- Read the entire label before using this product.
- Dispense 0.8 mL of product onto wet palm.
- Rub hands together to distribute product, then rinse hands with clean.

Antimicrobial Foam

Inactive Ingredients

Water, Potasium cocoate (contains coconut), Propylene Glycol, Glycerine, DMDM Hydantoin, Fragrance, FD&C Yellow #5, Aloe Barbadensis Leaf Juice. FD&C Red #40.

Antimicrobial Foam

Purpose

Antibacterial

Antimicrobial Foam

KEEP OUT OF REACH OF CHILDREN

Antimicrobial Foam

AFFEX CLEANING SOLUTIONS

Antimicrobial Foam Soap

Foaming Skin Cleanser with Triclosan

MEDICAL EMERGENCY:

(800)424-9300

NET CONTENTS: 1000 mL

ITEM #305-60